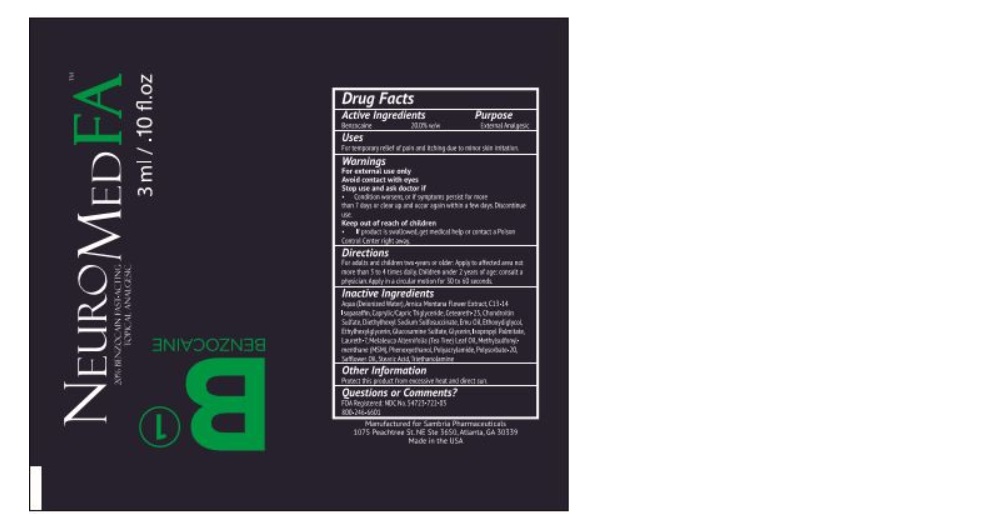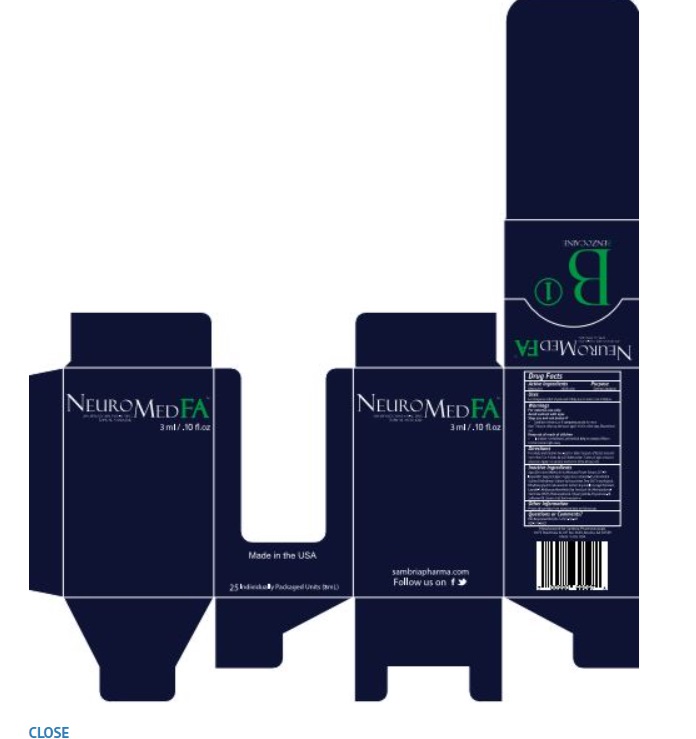 DRUG LABEL: NeuroMed



NDC: 54723-722 | Form: CREAM
Manufacturer: Sambria Pharmaceuticals, Inc.
Category: otc | Type: HUMAN OTC DRUG LABEL
Date: 20251112

ACTIVE INGREDIENTS: BENZOCAINE 20 mg/100 mg
INACTIVE INGREDIENTS: WATER; ARNICA MONTANA FLOWER; C13-14 ISOPARAFFIN; MEDIUM-CHAIN TRIGLYCERIDES; CETEARETH-25; CHONDROITIN SULFATE SODIUM (BOVINE); DOCUSATE SODIUM; EMU OIL; DIETHYLENE GLYCOL MONOETHYL ETHER; ETHYLHEXYLGLYCERIN; GLUCOSAMINE SULFATE; GLYCERIN; ISOPROPYL PALMITATE; LAURETH-7; MELALEUCA ALTERNIFOLIA LEAF; DIMETHYL SULFONE; PHENOXYETHANOL; POLYACRYLAMIDE (10000 MW); POLYSORBATE 20; SAFFLOWER OIL; STEARIC ACID; TROLAMINE

NeuroMed FA Topical Analgesic

Active Ingredients

Benzocaine 20.0% w/w

Purpose

External Analgesic

Uses

For temporary relief of pain and itching due to minor skin irritation.

Warnings

For external use only

Avoid contact with eyes

Stop use and ask doctor if

• Condition worsens, or if symptoms persist for more then 7 days or clear up and occur again within a few days. Discontinue use.

Keep out of reach of children

• If product is swallowed, get medical help or contact a Poison Control Center right away.

Directions

For adults and children two-years or older: Apply to affected area not more then 3 or 4 times daily. Children under 2 years of age: consult a physician.

Inactive Ingredients

Aqua (Deionized Water), Arnica Montana Flower Extract, C13-14 Isoparaffin, Caprylic/Capric Triglyceride, Cetearetj-25, Chondroitin Sulfate, Diethylhexyl Sodium Sulfosuccinate, Emu Oil, Ethoxydiglycol, Ethylhexylglycerin, Glucosamine Sulfate, Glycerin, Isopropyl Palmitate, Laureth-7, Melaleuca alternifolia (Tea Tree) Leaf Oil, Methylfulfonylmenthane (MSM), Phenoxyethanol, Polyacrylamide, Polysorbate-20, Safflower Oil, Stearic Acid, Triethanolamine

Other Information

Protect this product from excessive heat or direct sun.

Questions or Comments?

FDA Registered: NDC No. 54723-668-03

800-759-6876